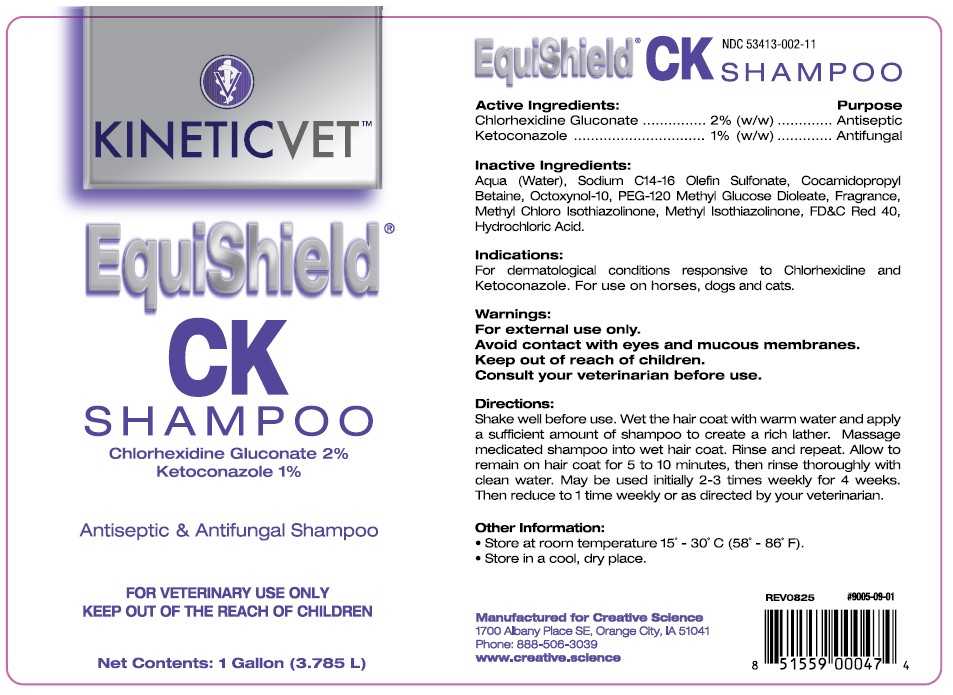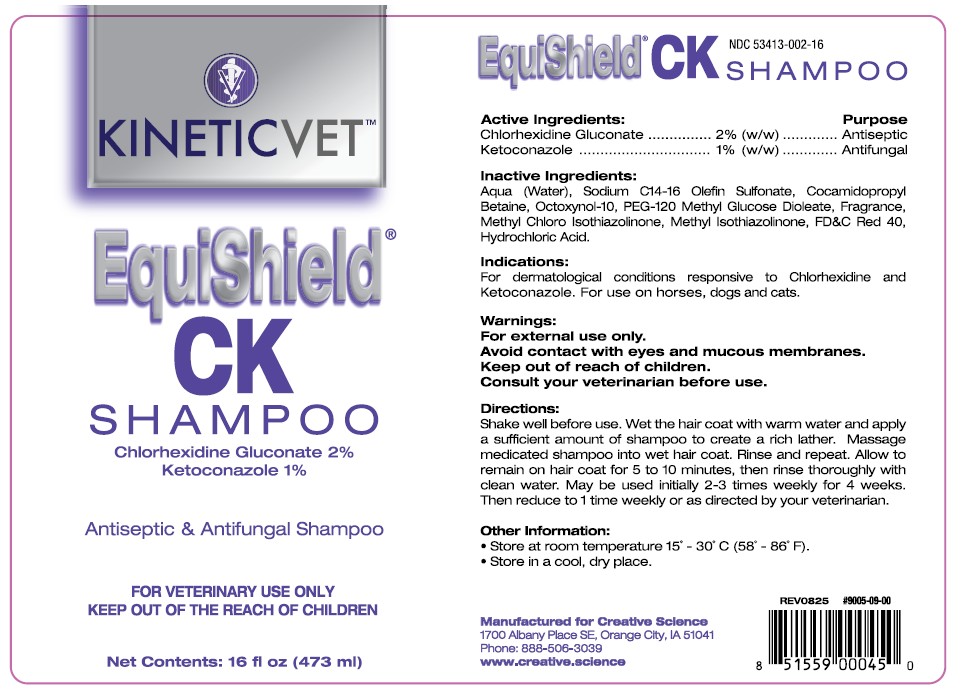 DRUG LABEL: EquiShield CK
NDC: 53413-002 | Form: SHAMPOO
Manufacturer: Creative Science
Category: animal | Type: OTC ANIMAL DRUG LABEL
Date: 20251229

ACTIVE INGREDIENTS: CHLORHEXIDINE GLUCONATE 2 g/100 mL; KETOCONAZOLE 1 g/100 mL

EquiShield® CK Shampoo

NDC 53413-002-11 (1 gallon)

NDC 53413-002-16 (16 oz)

Active Ingredients:

Chlorhexidine Gluconate .................. 2% (w/w)

Ketoconazole .................................. 1% (w/w)

Purpose

............. Antiseptic

............. Antifungal

Inactive Ingredients:

Aqua (Water), Sodium C14-16 Olefin Sulfonate, Cocamidopropyl Betaine, Octoxynol-10, PEG-120 Methyl Glucose Dioleate, Fragrance, Methyl Chloro Isothiazolinone, Methyl Isothiazolinone, FD&C Red 40, Hydrochloric Acid.

Indications:

For dermatological conditions reponsive to Chlorhexidine and Ketoconazole. For use on horses, dogs and cats.

Warnings:

For external use only.

Avoid contact with eyes and mucous membranes.

Keep out of reach of children.

Consult your veterinarian before use.

Directions:

Shake well before use. Wet the hair coat with warm water and apply a sufficient amount of shampoo to create a rich lather. Massage medicated shampoo into wet hair coat. Rinse and repeat. Allow to remain on hair coat for 5 to 10 minutes, then rinse thoroughly with clean water. May be used initially 2-3 times weekly for 4 weeks. Then reduce to 1 time weekly or as directed by your veterinarian.

Other Information:

- Store at room temperature 15° - 30° C (58° - 86 F).
- Store in a cool, dry place.

Manufactured for Creative Science

1700 Albany Place SE, Orange City, IA 51041

Phone: 888-506-3039

www.creative.science

REV0825 #9005-09-01 UPC 851559000474 (1 gallon)

REV0825 #9005-09-00 UPC 851559000450 (16 oz)

PACKAGE LABEL

Chlorhexidine Gluconate 2%

Ketoconazole 1%

Antiseptic & Antifungal Shampoo

FOR VETERINARY USE ONLY

KEEP OUT OF THE REACH OF CHILDREN

Net Contents: 16 fl oz (473 ml)

Chlorhexidine Gluconate 2%

Ketoconazole 1%

Antiseptic & Antifungal Shampoo

FOR VETERINARY USE ONLY

KEEP OUT OF THE REACH OF CHILDREN

Net Contents: 1 Gallon (3.785 L)